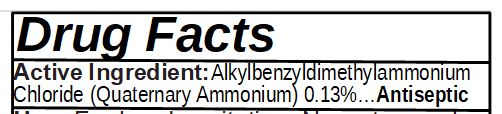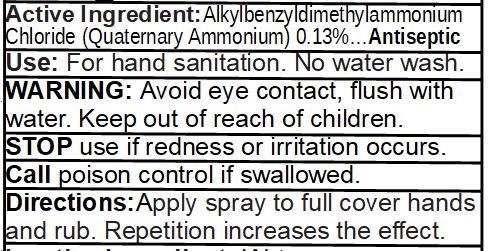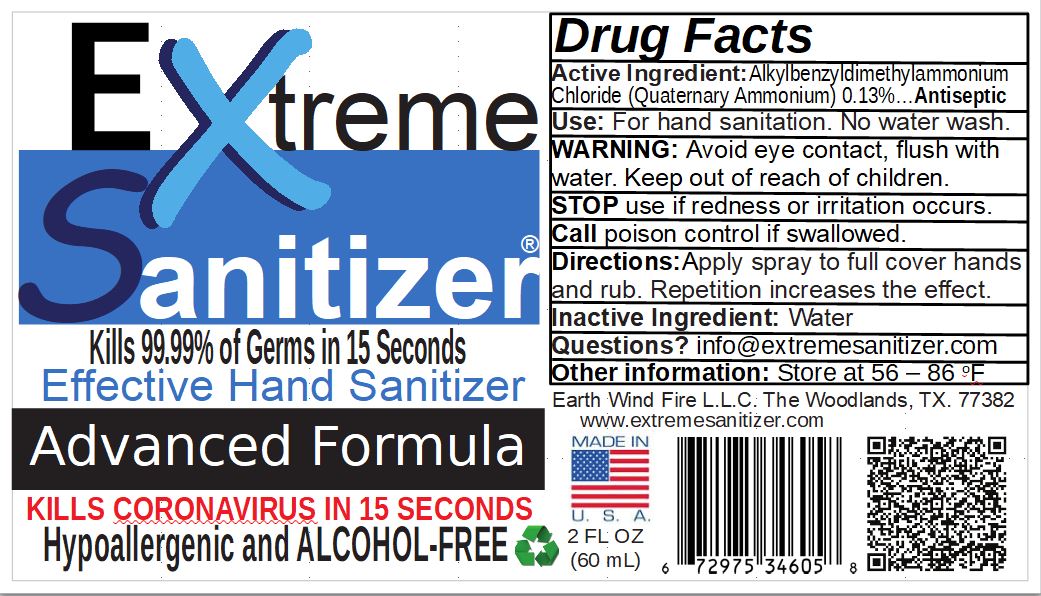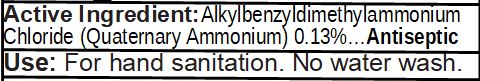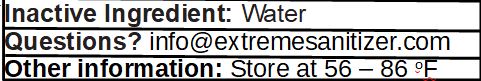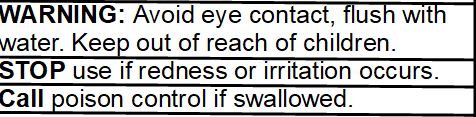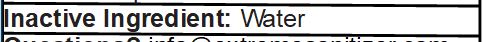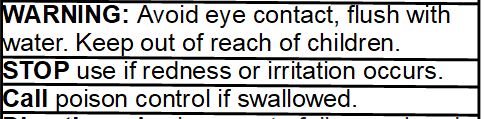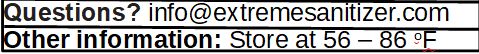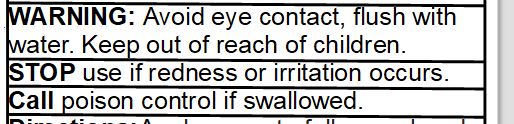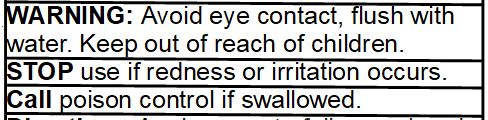 DRUG LABEL: Extreme Sanitizer
NDC: 77868-0001 | Form: LIQUID
Manufacturer: Earth Wind Fire L.L.C. / Extreme Sanitizer®
Category: otc | Type: HUMAN OTC DRUG LABEL
Date: 20201228

ACTIVE INGREDIENTS: BENZALKONIUM CHLORIDE 1.3 mg/1 mL
INACTIVE INGREDIENTS: WATER

Extreme Hand Sanitizer®

Extreme Sanitizer®

Kills 99.99% of Germs in 15 Seconds

Effective Hand Sanitizer

Advanced Formula

KILLS CORONAVIRUS IN 15 SECONDS

Hypoallergenic and ALCOHOL-FREE

Drug Facts

Active Ingredient:Alkylbenzyldimethylammonium
Chloride (Quaternary Ammonium) 0.13%…Antiseptic
Use: For hand sanitation. No water wash.
WARNING: Avoid eye contact, flush with
water. Keep out of reach of children.
STOP use if redness or irritation occurs.
Call poison control if swallowed.
Directions:Apply spray to full cover hands
and rub. Repetition increases the effect.
Inactive Ingredient: Water
Questions? info@extremesanitizer.com
Other information: Store at 56 – 86 oF

Earth Wind Fire L.L.C. The Woodlands, TX. 77382

www.extremesanitizer.com

2 FL OZ
(60 mL)

Active Ingredient

Active Ingredient:Alkylbenzyldimethylammonium
Chloride (Quaternary Ammonium) 0.13%…Antiseptic

Dosage and administration

Active Ingredient:Alkylbenzyldimethylammonium
Chloride (Quaternary Ammonium) 0.13%…Antiseptic

Use: For hand sanitation. No water wash.

Directions:Apply spray to full cover hands
and rub. Repetition increases the effect.

Warning

WARNING: Avoid eye contact, flush with
water. Keep out of reach of children.

Other Information

Other information: Store at 56 – 86 oF

Questions

Questions? info@extremesanitizer.com

Use and Purpose

Antiseptic
Use: For hand sanitation. No water wash.

Warning

WARNING: Avoid eye contact, flush with
water. Keep out of reach of children.

Do Not Use Stop Use

WARNING: Avoid eye contact, flush with
water. Keep out of reach of children.
STOP use if redness or irritation occurs.
Call poison control if swallowed.

Stop Use

WARNING: Avoid eye contact, flush with
water. Keep out of reach of children.
STOP use if redness or irritation occurs.
Call poison control if swallowed.

Warning

WARNING: Avoid eye contact, flush with
water. Keep out of reach of children.

Stop Use

STOP use if redness or irritation occurs.
Call poison control if swallowed.

Indication and Usage

Use: For hand sanitation. No water wash.

Directions:Apply spray to full cover hands
and rub. Repetition increases the effect.

Inactive Ingredients

Inactive Ingredient: Water